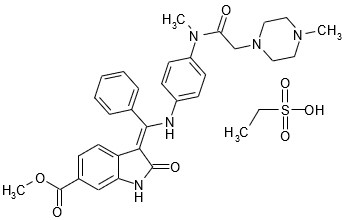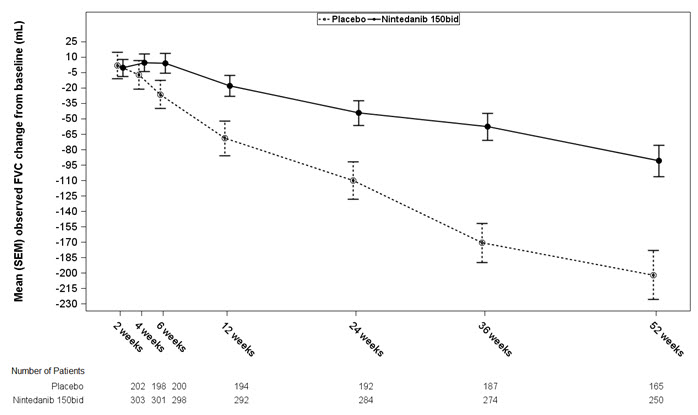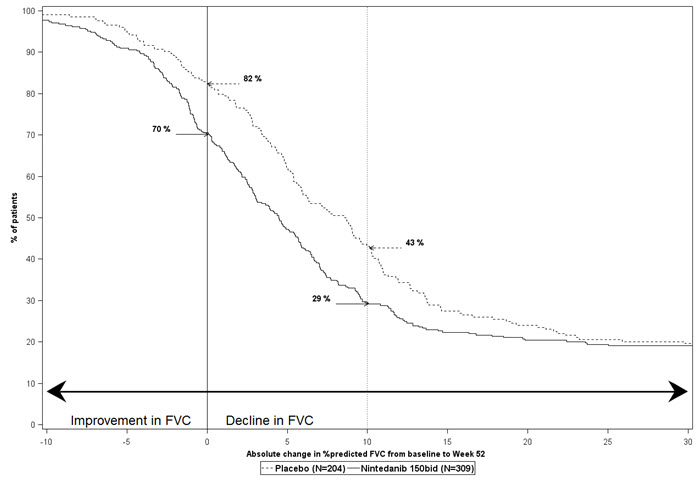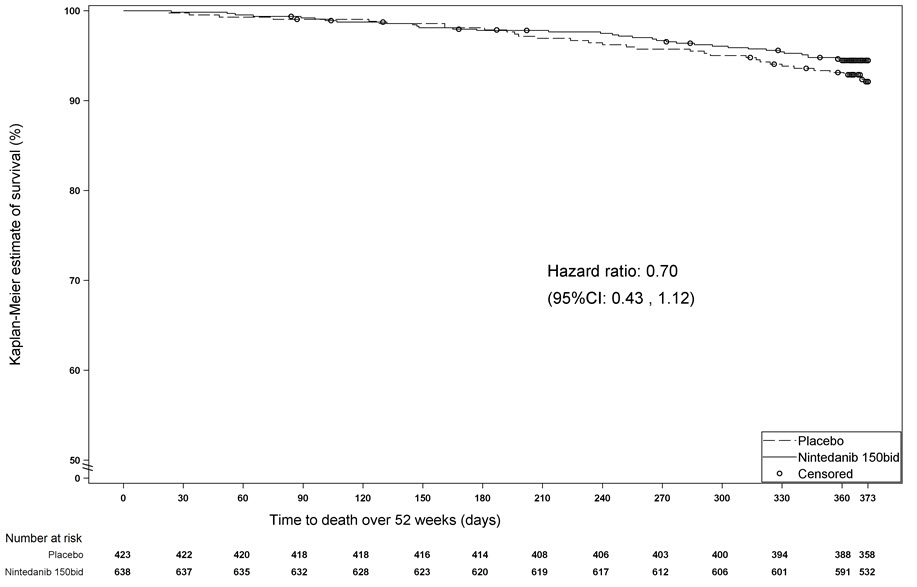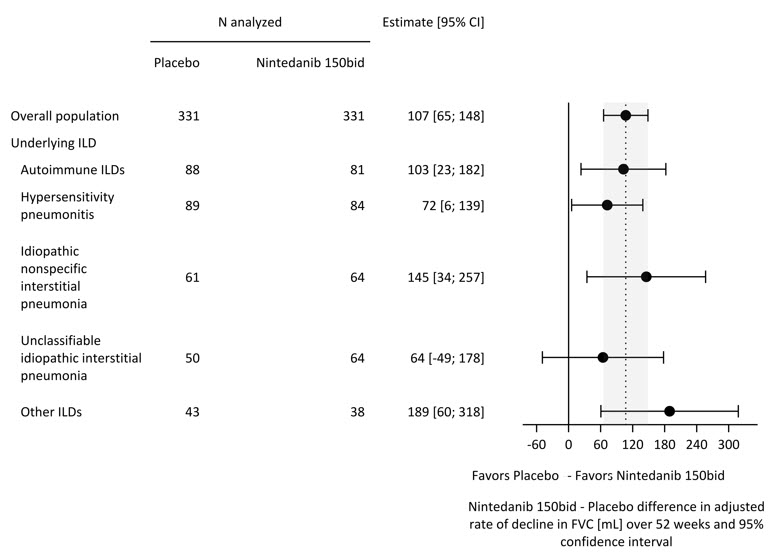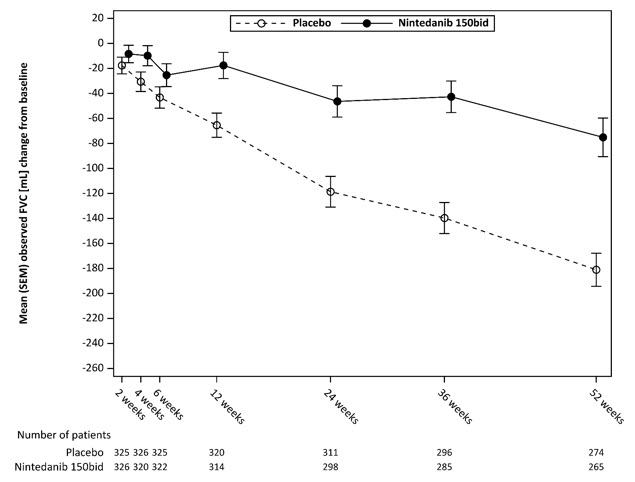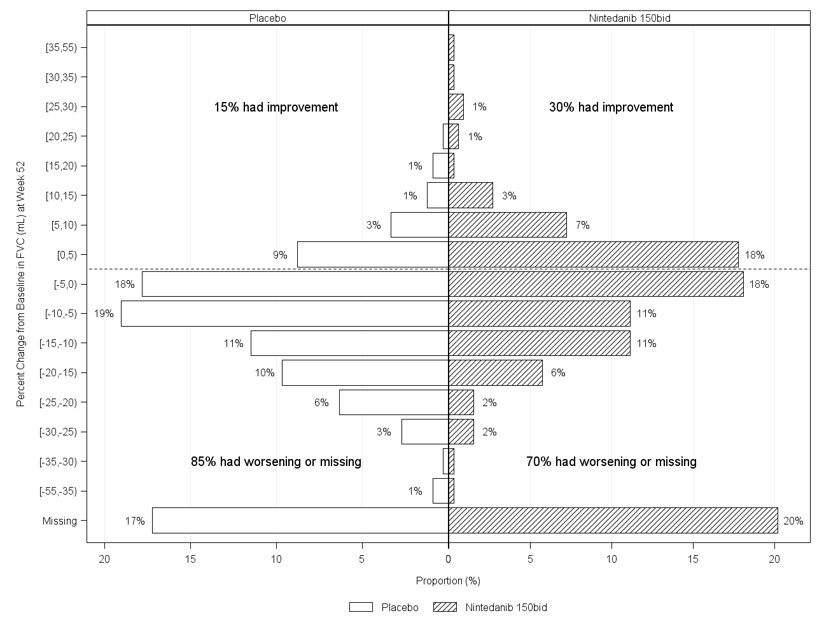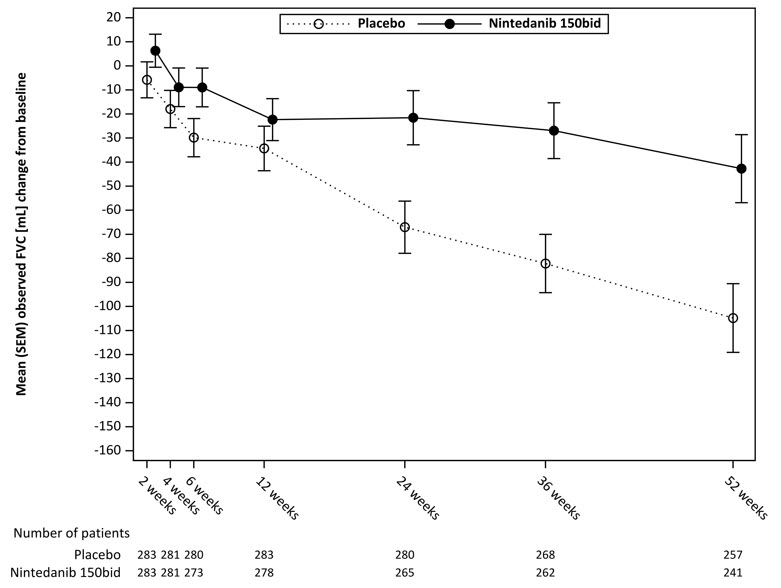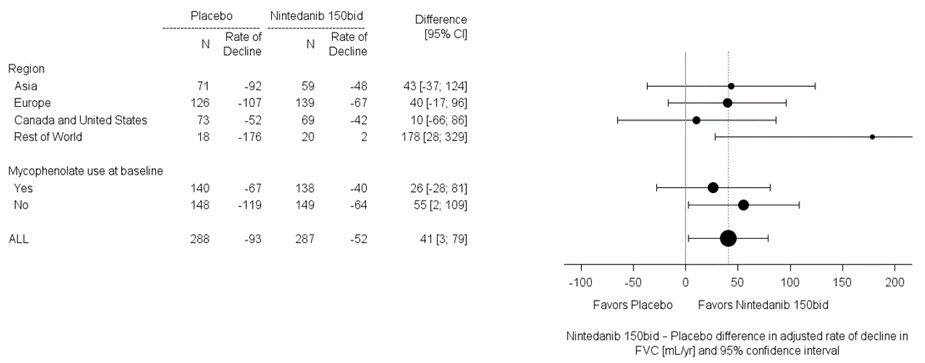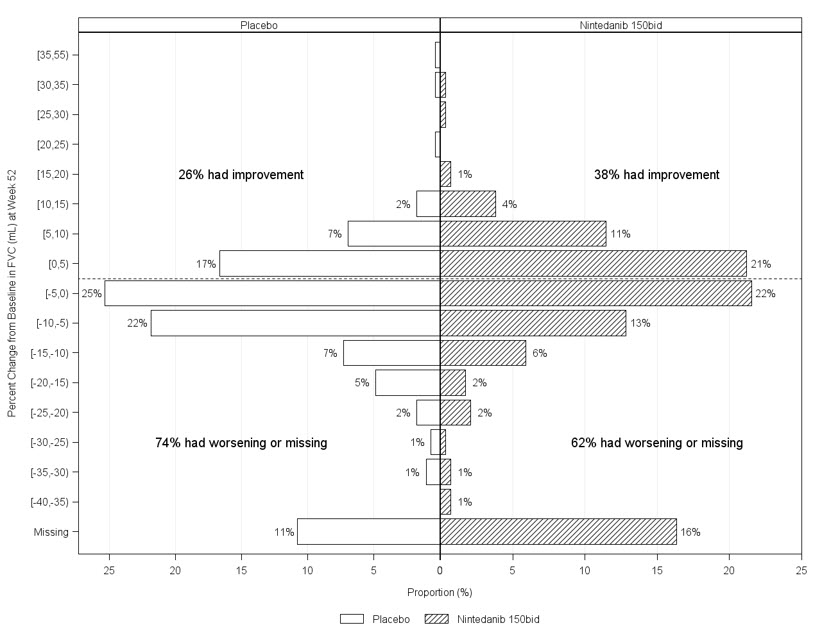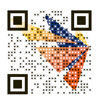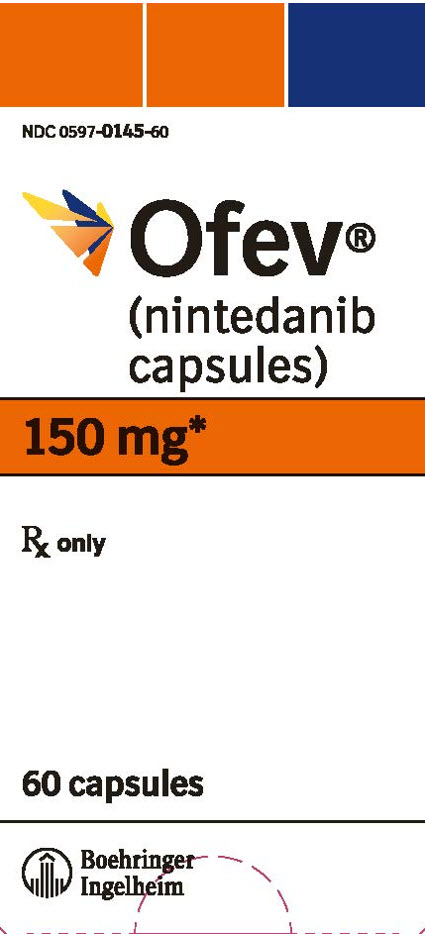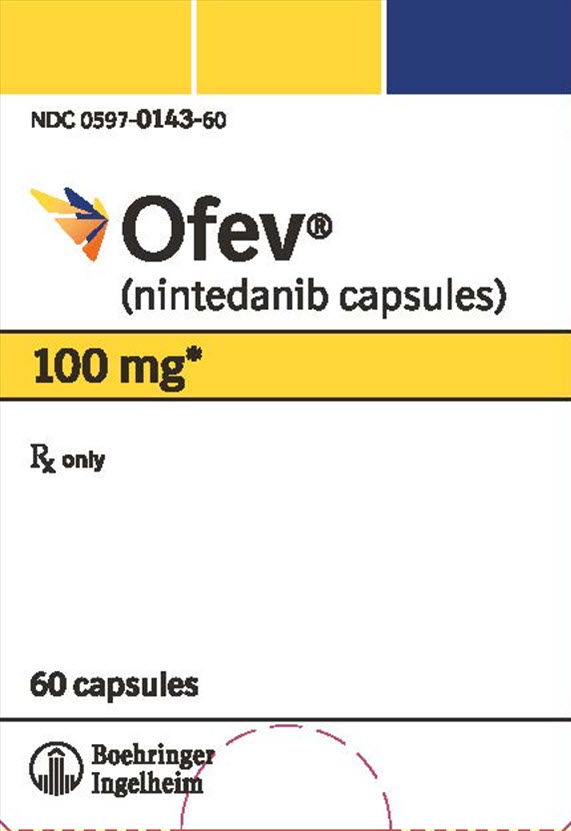 DRUG LABEL: Ofev
NDC: 0597-0145 | Form: CAPSULE
Manufacturer: Boehringer Ingelheim Pharmaceuticals, Inc.
Category: prescription | Type: HUMAN PRESCRIPTION DRUG LABEL
Date: 20251120

ACTIVE INGREDIENTS: NINTEDANIB ESYLATE 150 mg/1 1

HIGHLIGHTS OF PRESCRIBING INFORMATION

These highlights do not include all the information needed to use OFEV safely and effectively. See full prescribing information for OFEV.
OFEV® (nintedanib capsules), for oral use
Initial U.S. Approval: 2014

1 INDICATIONS AND USAGE

OFEV is a kinase inhibitor indicated in adults for:

- Treatment of idiopathic pulmonary fibrosis (IPF) (1.1)
- Treatment of chronic fibrosing interstitial lung diseases (ILDs) with a progressive phenotype (1.2)
- Slowing the rate of decline in pulmonary function in patients with systemic sclerosis-associated interstitial lung disease (SSc-ILD) (1.3)

2 DOSAGE AND ADMINISTRATION

- Recommended dosage: 150 mg taken orally twice daily approximately 12 hours apart taken with food. (2.2)
- Recommended dosage in patients with mild hepatic impairment (Child Pugh A): 100 mg taken orally twice daily approximately 12 hours apart taken with food. (2.3, 8.6)
- Consider temporary dose reduction to 100 mg, treatment interruption, or discontinuation for management of adverse reactions. (2.4, 5.2, 5.3, 6)
- Prior to treatment initiation, conduct liver function tests in all patients and a pregnancy test in females of reproductive potential. (2.1, 5.2, 5.4)

3 DOSAGE FORMS AND STRENGTHS

Capsules: 150 mg and 100 mg (3)

4 CONTRAINDICATIONS

None (4)

5 WARNINGS AND PRECAUTIONS

- Hepatic impairment: OFEV is not recommended for use in patients with moderate or severe hepatic impairment. In patients with mild hepatic impairment (Child Pugh A), the recommended dosage is 100 mg twice daily approximately 12 hours apart taken with food. Consider treatment interruption, or discontinuation for management of adverse reactions in these patients. (2.3, 2.4, 5.1, 8.6, 12.3)
- Elevated liver enzymes and drug-induced liver injury: ALT, AST, and bilirubin elevations have occurred with OFEV, including cases of drug-induced liver injury. In the postmarketing period, non-serious and serious cases of drug-induced liver injury, including severe liver injury with fatal outcome, have been reported. The majority of hepatic events occur within the first three months of treatment. Liver enzyme and bilirubin increases were reversible with dose modification or interruption in the majority of cases. Monitor ALT, AST, and bilirubin prior to initiation of treatment, at regular intervals during the first three months of treatment, and periodically thereafter or as clinically indicated. Temporary dosage reductions or discontinuations may be required. (2.1, 2.4, 5.2)
- Gastrointestinal disorders: Diarrhea, nausea, and vomiting have occurred with OFEV. Treat patients at first signs with adequate hydration and antidiarrheal medicine (e.g., loperamide) or anti-emetics. Discontinue OFEV if severe diarrhea, nausea, or vomiting persists despite symptomatic treatment. (5.3)
- Embryo-Fetal toxicity: Can cause fetal harm. Advise females of reproductive potential of the potential risk to a fetus and to use highly effective contraception. Advise women taking oral hormonal contraceptives experiencing vomiting, diarrhea, or other conditions where the drug absorption may be reduced to use alternative highly effective contraception. (5.4, 8.1, 8.3)
- Arterial thromboembolic events have been reported. Use caution when treating patients at higher cardiovascular risk including known coronary artery disease. (5.5)
- Bleeding events have been reported. Use OFEV in patients with known bleeding risk only if anticipated benefit outweighs the potential risk. (5.6)
- Gastrointestinal perforation has been reported. Use OFEV with caution when treating patients with recent abdominal surgery, previous history of diverticular disease or receiving concomitant corticosteroids or NSAIDs. Discontinue OFEV in patients who develop gastrointestinal perforation. Only use OFEV in patients with known risk of gastrointestinal perforation if the anticipated benefit outweighs the potential risk. (5.7)
- Nephrotic range proteinuria has been reported. Consider treatment interruption in patients who develop new or worsening proteinuria. (5.8)

6 ADVERSE REACTIONS

Most common adverse reactions (≥5%) are: diarrhea, nausea, abdominal pain, vomiting, liver enzyme elevation, decreased appetite, headache, weight decreased, and hypertension. (6.1)

To report SUSPECTED ADVERSE REACTIONS, contact Boehringer Ingelheim Pharmaceuticals, Inc. at (800) 542-6257 or FDA at 1-800-FDA-1088 or www.fda.gov/medwatch.

7 DRUG INTERACTIONS

- Coadministration of P-gp and CYP3A4 inhibitors may increase nintedanib exposure. Monitor patients closely for tolerability of OFEV. (7.1)

8 USE IN SPECIFIC POPULATIONS

- Lactation: Breastfeeding is not recommended. (8.2)
- Renal impairment: The safety and efficacy of OFEV have not been studied in patients with severe renal impairment and end-stage renal disease. (8.7, 12.3)
- Smokers: Decreased exposure has been noted in smokers which may alter the efficacy profile of OFEV. (8.8)

FULL PRESCRIBING INFORMATION

1 INDICATIONS AND USAGE

1.1 Idiopathic Pulmonary Fibrosis

OFEV is indicated for the treatment of adults with idiopathic pulmonary fibrosis (IPF).

1.2 Chronic Fibrosing Interstitial Lung Diseases with a Progressive Phenotype

OFEV is indicated for the treatment of adults with chronic fibrosing interstitial lung diseases (ILDs) with a progressive phenotype [see Clinical Studies (14.2)].

1.3 Systemic Sclerosis-Associated Interstitial Lung Disease

OFEV is indicated to slow the rate of decline in pulmonary function in adult patients with systemic sclerosis-associated interstitial lung disease (SSc-ILD).

2 DOSAGE AND ADMINISTRATION

2.1 Testing Prior to OFEV Administration

Conduct liver function tests in all patients and a pregnancy test in females of reproductive potential prior to initiating treatment with OFEV [see Warnings and Precautions (5.2, 5.4)].

2.2 Recommended Dosage

The recommended dosage of OFEV is 150 mg taken orally twice daily administered approximately 12 hours apart.

Administration Information

OFEV capsules should be taken with food [see Clinical Pharmacology (12.3)] and swallowed whole with liquid. OFEV capsules should not be chewed because of a bitter taste.

OFEV capsules should not be opened or crushed. If contact with the content of the capsule occurs, wash hands immediately and thoroughly. The effect of chewing or crushing of the capsule on the pharmacokinetics of nintedanib is not known.

Information for Missed Dose

If a dose of OFEV is missed, the next dose should be taken at the next scheduled time. Advise the patient to not make up for a missed dose. Do not exceed the recommended maximum daily dosage of 300 mg.

2.3 Recommended Dosage for Patients with Hepatic Impairment

Mild Hepatic Impairment

In patients with mild hepatic impairment (Child Pugh A), the recommended dosage of OFEV is 100 mg orally twice daily approximately 12 hours apart taken with food [see Use in Specific Populations (8.6)].

Moderate or Severe Hepatic Impairment

Treatment with OFEV is not recommended [see Warnings and Precautions (5.1) and Use in Specific Populations (8.6)].

2.4 Dosage Modification due to Adverse Reactions

In addition to symptomatic treatment, if applicable, the management of adverse reactions of OFEV may require dose reduction or temporary interruption until the specific adverse reaction resolves to levels that allow continuation of therapy. OFEV treatment may be resumed at the full dosage (150 mg twice daily), or at the reduced dosage (100 mg twice daily), which subsequently may be increased to the full dosage. If a patient does not tolerate 100 mg twice daily, discontinue treatment with OFEV [see Warnings and Precautions (5.2, 5.3, 5.5, 5.7) and Adverse Reactions (6.1)].

Elevated Liver Enzymes

Dose modifications or interruptions may be necessary for liver enzyme elevations. Conduct liver function tests (aspartate aminotransferase (AST), alanine aminotransferase (ALT), and bilirubin) prior to initiation of treatment with OFEV, at regular intervals during the first three months of treatment, and periodically thereafter or as clinically indicated. Measure liver tests promptly in patients who report symptoms that may indicate liver injury, including fatigue, anorexia, right upper abdominal discomfort, dark urine or jaundice. Discontinue OFEV in patients with AST or ALT greater than 3 times the upper limit of normal (ULN) with signs or symptoms of liver injury and for AST or ALT elevations greater than 5 times the upper limit of normal. For AST or ALT greater than 3 times to less than 5 times the ULN without signs of liver damage, interrupt treatment or reduce OFEV to 100 mg twice daily. Once liver enzymes have returned to baseline values, treatment with OFEV may be reintroduced at a reduced dosage (100 mg twice daily), which subsequently may be increased to the full dosage (150 mg twice daily) [see Warnings and Precautions (5.2) and Adverse Reactions (6.1)].

In patients with mild hepatic impairment (Child Pugh A), consider treatment interruption, or discontinuation for management of adverse reactions.

3 DOSAGE FORMS AND STRENGTHS

Capsules:

- 150 mg, brown, opaque, oblong, soft capsules marked in dark gray with the Boehringer Ingelheim company symbol and "150".
- 100 mg, peach, opaque, oblong, soft capsules marked in dark gray with the Boehringer Ingelheim company symbol and "100".

4 CONTRAINDICATIONS

None

5 WARNINGS AND PRECAUTIONS

5.1 Hepatic Impairment

Treatment with OFEV is not recommended in patients with moderate (Child Pugh B) or severe (Child Pugh C) hepatic impairment [see Use in Specific Populations (8.6) and Clinical Pharmacology (12.3)]. Patients with mild hepatic impairment (Child Pugh A) can be treated with a reduced dose of OFEV [see Dosage and Administration (2.3)].

5.2 Elevated Liver Enzymes and Drug-Induced Liver Injury

Cases of drug-induced liver injury (DILI) have been observed with OFEV treatment. In the clinical trials and postmarketing period, non-serious and serious cases of DILI were reported. Cases of severe liver injury with fatal outcome have been reported in the postmarketing period. The majority of hepatic events occur within the first three months of treatment. In clinical trials, administration of OFEV was associated with elevations of liver enzymes (ALT, AST, ALKP, GGT) and bilirubin. Liver enzyme and bilirubin increases were reversible with dose modification or interruption in the majority of cases. In IPF studies (Study 1, Study 2, and Study 3), the majority (94%) of patients with ALT and/or AST elevations had elevations less than 5 times ULN and the majority (95%) of patients with bilirubin elevations had elevations less than 2 times ULN. In the chronic fibrosing ILDs with a progressive phenotype study (Study 5), the majority (95%) of patients with ALT and/or AST elevations had elevations less than 5 times ULN and the majority (94%) of patients with bilirubin elevations had elevations less than 2 times ULN. In the SSc-ILD study (Study 4), a maximum ALT and/or AST greater than or equal to 3 times ULN was observed for 4.9% of patients in the OFEV group and for 0.7% of patients in the placebo group [see Use in Specific Populations (8.6) and Clinical Pharmacology (12.3)]. Patients with a low body weight (less than 65 kg), Asian, and female patients may have a higher risk of elevations in liver enzymes. Nintedanib exposure increased with patient age, which may also result in a higher risk of increased liver enzymes [see Clinical Pharmacology (12.3)].

Conduct liver function tests (ALT, AST, and bilirubin) prior to initiation of treatment with OFEV, at regular intervals during the first three months of treatment, and periodically thereafter or as clinically indicated. Measure liver tests promptly in patients who report symptoms that may indicate liver injury, including fatigue, anorexia, right upper abdominal discomfort, dark urine or jaundice. Dosage modifications or interruption may be necessary for liver enzyme elevations [see Dosage and Administration (2.1, 2.4)].

5.3 Gastrointestinal Disorders

Diarrhea

In clinical trials, diarrhea was the most frequent gastrointestinal event reported. In most patients, the event was of mild to moderate intensity and occurred within the first 3 months of treatment. In IPF studies (Study 1, Study 2, and Study 3), diarrhea was reported in 62% versus 18% of patients treated with OFEV and placebo, respectively [see Adverse Reactions (6.1)]. Diarrhea led to permanent dose reduction in 11% of patients treated with OFEV compared to 0 placebo-treated patients. Diarrhea led to discontinuation of OFEV in 5% of the patients compared to less than 1% of placebo-treated patients. In the chronic fibrosing ILDs with a progressive phenotype study (Study 5), diarrhea was reported in 67% versus 24% of patients treated with OFEV and placebo, respectively [see Adverse Reactions (6.1)]. Diarrhea led to permanent dose reduction in 16% of patients treated with OFEV compared to less than 1% of placebo-treated patients. Diarrhea led to discontinuation of OFEV in 6% of the patients compared to less than 1% of placebo-treated patients. In the SSc-ILD study (Study 4), diarrhea was reported in 76% versus 32% of patients treated with OFEV and placebo, respectively [see Adverse Reactions (6.1)]. Diarrhea led to permanent dose reduction in 22% of patients treated with OFEV compared to 1% of placebo-treated patients. Diarrhea led to discontinuation of OFEV in 7% of the patients compared to 0.3% of placebo-treated patients.

Dosage modifications or treatment interruptions may be necessary in patients with adverse reactions of diarrhea. Treat diarrhea at first signs with adequate hydration and antidiarrheal medication (e.g., loperamide), and consider dose reduction or treatment interruption if diarrhea continues [see Dosage and Administration (2.4)]. OFEV treatment may be resumed at the full dosage (150 mg twice daily), or at the reduced dosage (100 mg twice daily), which subsequently may be increased to the full dosage. If severe diarrhea persists despite symptomatic treatment, discontinue treatment with OFEV.

Nausea and Vomiting

In IPF studies (Study 1, Study 2, and Study 3), nausea was reported in 24% versus 7% and vomiting was reported in 12% versus 3% of patients treated with OFEV and placebo, respectively. In the chronic fibrosing ILDs with a progressive phenotype study (Study 5), nausea was reported in 29% versus 9% and vomiting was reported in 18% versus 5% of patients treated with OFEV and placebo, respectively. In the SSc-ILD study (Study 4), nausea was reported in 32% versus 14% and vomiting was reported in 25% versus 10% of patients treated with OFEV and placebo, respectively [see Adverse Reactions (6.1)]. In most patients, these events were of mild to moderate intensity. In IPF studies (Study 1, Study 2, and Study 3), nausea led to discontinuation of OFEV in 2% of patients and vomiting led to discontinuation of OFEV in 1% of the patients. In the chronic fibrosing ILDs with a progressive phenotype study (Study 5), nausea led to discontinuation of OFEV in less than 1% of patients and vomiting led to discontinuation of OFEV in 1% of the patients. In the SSc-ILD study (Study 4), nausea led to discontinuation of OFEV in 2% of patients and vomiting led to discontinuation of OFEV in 1% of the patients.

For nausea or vomiting that persists despite appropriate supportive care including anti-emetic therapy, dose reduction or treatment interruption may be required [see Dosage and Administration (2.4)]. OFEV treatment may be resumed at the full dosage (150 mg twice daily), or at the reduced dosage (100 mg twice daily), which subsequently may be increased to the full dosage. If severe nausea or vomiting does not resolve, discontinue treatment with OFEV.

5.4 Embryo-Fetal Toxicity

Based on findings from animal studies and its mechanism of action, OFEV can cause fetal harm when administered to a pregnant woman. Nintedanib caused embryo-fetal deaths and structural abnormalities in rats and rabbits when administered during organogenesis at less than (rats) and approximately 5 times (rabbits) the maximum recommended human dose (MRHD) in adults. Advise pregnant women of the potential risk to a fetus. Advise females of reproductive potential to avoid becoming pregnant while receiving treatment with OFEV and to use highly effective contraception at initiation of, during treatment, and at least 3 months after the last dose of OFEV. Nintedanib does not change the exposure to oral contraceptive containing ethinylestradiol and levonorgestrel in patients with SSc-ILD. However, the efficacy of oral hormonal contraceptives may be compromised by vomiting and/or diarrhea or other conditions where the drug absorption may be reduced. Advise women taking oral hormonal contraceptives experiencing these conditions to use alternative highly effective contraception. Verify pregnancy status prior to treatment with OFEV and during treatment as appropriate [see Use in Specific Populations (8.1, 8.3) and Clinical Pharmacology (12.1, 12.3)].

5.5 Arterial Thromboembolic Events

Arterial thromboembolic events have been reported in patients taking OFEV. In IPF studies (Study 1, Study 2, and Study 3), arterial thromboembolic events were reported in 2.5% of patients treated with OFEV and less than 1% of placebo-treated patients. Myocardial infarction was the most common adverse reaction under arterial thromboembolic events, occurring in 1.5% of OFEV-treated patients compared to less than 1% of placebo-treated patients. In the chronic fibrosing ILDs with a progressive phenotype study (Study 5), arterial thromboembolic events were reported in less than 1% of patients in both treatment arms. Myocardial infarction was observed in less than 1% of patients in both treatment arms. In the SSc-ILD study (Study 4), arterial thromboembolic events were reported in 0.7% of patients in both treatment arms. There were 0 cases of myocardial infarction in OFEV-treated patients compared to 0.7% of placebo-treated patients.

Use caution when treating patients at higher cardiovascular risk including known coronary artery disease. Consider treatment interruption in patients who develop signs or symptoms of acute myocardial ischemia.

5.6 Risk of Bleeding

Based on the mechanism of action (VEGFR inhibition), OFEV may increase the risk of bleeding. In IPF studies (Study 1, Study 2, and Study 3), bleeding events were reported in 10% of patients treated with OFEV and in 7% of patients treated with placebo. In the chronic fibrosing ILDs with a progressive phenotype study (Study 5), bleeding events were reported in 11% of patients treated with OFEV and in 13% of patients treated with placebo. In the SSc-ILD study (Study 4), bleeding events were reported in 11% of patients treated with OFEV and in 8% of patients treated with placebo. In clinical trials, epistaxis was the most frequent bleeding event reported.

In the postmarketing period non-serious and serious bleeding events, some of which were fatal, have been observed.

Use OFEV in patients with known risk of bleeding only if the anticipated benefit outweighs the potential risk.

5.7 Gastrointestinal Perforation

Based on the mechanism of action, OFEV may increase the risk of gastrointestinal perforation. In IPF studies (Study 1, Study 2, and Study 3), gastrointestinal perforation was reported in less than 1% of patients treated with OFEV, compared to 0 cases in the placebo-treated patients. In the chronic fibrosing ILDs with a progressive phenotype study (Study 5), gastrointestinal perforation was not reported in any patients in any treatment arm. In the SSc-ILD study (Study 4), no cases of gastrointestinal perforation were reported in patients treated with OFEV or in placebo-treated patients.

In the postmarketing period, cases of gastrointestinal perforations have been reported, some of which were fatal.

Use caution when treating patients who have had recent abdominal surgery, previous history of diverticular disease or receiving concomitant corticosteroids or NSAIDs. Discontinue therapy with OFEV in patients who develop gastrointestinal perforation. Only use OFEV in patients with known risk of gastrointestinal perforation if the anticipated benefit outweighs the potential risk.

5.8 Nephrotic Range Proteinuria

Cases of proteinuria within the nephrotic range have been reported in the postmarketing period. Histological findings, when available, were consistent with glomerular microangiopathy with or without renal thrombi. Improvement in proteinuria has been observed after OFEV was discontinued; however, in some cases, residual proteinuria persisted. Consider treatment interruption in patients who develop new or worsening proteinuria.

6 ADVERSE REACTIONS

The following clinically significant adverse reactions are discussed in greater detail in other sections of the labeling:

- Elevated Liver Enzymes and Drug-Induced Liver Injury [see Warnings and Precautions (5.2)]
- Gastrointestinal Disorders [see Warnings and Precautions (5.3)]
- Embryo-Fetal Toxicity [see Warnings and Precautions (5.4)]
- Arterial Thromboembolic Events [see Warnings and Precautions (5.5)]
- Risk of Bleeding [see Warnings and Precautions (5.6)]
- Gastrointestinal Perforation [see Warnings and Precautions (5.7)]
- Nephrotic Range Proteinuria [see Warnings and Precautions (5.8)]

6.1 Clinical Trials Experience

Because clinical trials are conducted under widely varying conditions, adverse reaction rates observed in the clinical trials of a drug cannot be directly compared to rates in the clinical trials of another drug and may not reflect the rates observed in practice.

The safety of OFEV was evaluated in over 1000 IPF patients, 332 patients with chronic fibrosing ILDs with a progressive phenotype, and over 280 patients with SSc-ILD. Over 200 IPF patients were exposed to OFEV for more than 2 years in clinical trials.

Idiopathic Pulmonary Fibrosis

OFEV was studied in three randomized, double-blind, placebo-controlled, 52-week trials. In the phase 2 (Study 1) and phase 3 (Study 2 and Study 3) trials, 723 patients with IPF received OFEV 150 mg twice daily and 508 patients received placebo. The median duration of exposure was 10 months for patients treated with OFEV and 11 months for patients treated with placebo. Subjects ranged in age from 42 to 89 years (median age of 67 years). Most patients were male (79%) and Caucasian (60%).

The most frequent serious adverse reactions reported in patients treated with OFEV, more than placebo, were bronchitis (1.2% vs. 0.8%) and myocardial infarction (1.5% vs. 0.4%). The most common adverse events leading to death in patients treated with OFEV, more than placebo, were pneumonia (0.7% vs. 0.6%), lung neoplasm malignant (0.3% vs. 0%), and myocardial infarction (0.3% vs. 0.2%). In the predefined category of major adverse cardiovascular events (MACE) including MI, fatal events were reported in 0.6% of OFEV-treated patients and 1.8% of placebo-treated patients.

Adverse reactions leading to permanent dose reductions were reported in 16% of OFEV-treated patients and 1% of placebo-treated patients. The most frequent adverse reaction that led to permanent dose reduction in the patients treated with OFEV was diarrhea (11%).

Adverse reactions leading to discontinuation were reported in 21% of OFEV-treated patients and 15% of placebo-treated patients. The most frequent adverse reactions that led to discontinuation in OFEV-treated patients were diarrhea (5%), nausea (2%), and decreased appetite (2%).

The most common adverse reactions with an incidence of greater than or equal to 5% and more frequent in the OFEV than placebo treatment group are listed in Table 1.

Table 1 Adverse Reactions Occurring in ≥5% of OFEV-treated Patients with Idiopathic Pulmonary Fibrosis and More Commonly Than Placebo in Study 1, Study 2, and Study 3
Adverse Reaction | OFEV, 150 mg n=723 | Placebo n=508
Gastrointestinal disorders
Diarrhea | 62% | 18%
Nausea | 24% | 7%
Abdominal paina | 15% | 6%
Vomiting | 12% | 3%
Hepatobiliary disorders
Liver enzyme elevationb | 14% | 3%
Metabolism and nutrition disorders
Decreased appetite | 11% | 5%
Nervous system disorders
Headache | 8% | 5%
Investigations
Weight decreased | 10% | 3%
Vascular disorders
Hypertensionc | 5% | 4%
a Includes abdominal pain, abdominal pain upper, abdominal pain lower, gastrointestinal pain and abdominal tenderness.
b Includes gamma-glutamyltransferase increased, hepatic enzyme increased, alanine aminotransferase increased, aspartate aminotransferase increased, hepatic function abnormal, liver function test abnormal, transaminase increased, blood alkaline phosphatase-increased, alanine aminotransferase abnormal, aspartate aminotransferase abnormal, and gamma-glutamyltransferase abnormal.
c Includes hypertension, blood pressure increased, hypertensive crisis, and hypertensive cardiomyopathy.

In addition, hypothyroidism was reported in patients treated with OFEV, more than placebo (1.1% vs. 0.6%). Alopecia was also reported in more patients treated with OFEV than placebo (0.8% vs. 0.4%).

Combination with Pirfenidone

Concomitant treatment with nintedanib and pirfenidone was investigated in an exploratory open-label, randomized (1:1) trial of nintedanib 150 mg twice daily with add-on pirfenidone (titrated to 801 mg three times a day) compared to nintedanib 150 mg twice daily alone in 105 randomized patients for 12 weeks. The primary endpoint was the percentage of patients with gastrointestinal adverse events from baseline to Week 12. Gastrointestinal adverse events were in line with the established safety profile of each component and were experienced in 37 (70%) patients treated with pirfenidone added to nintedanib versus 27 (53%) patients treated with nintedanib alone.

Diarrhea, nausea, vomiting, and abdominal pain (includes upper abdominal pain, abdominal discomfort, and abdominal pain) were the most frequent adverse events reported in 20 (38%) versus 16 (31%), in 22 (42%) versus 6 (12%), in 15 (28%) versus 6 (12%), and in 15 (28%) versus 7 (14%) patients treated with pirfenidone added to nintedanib versus nintedanib alone, respectively. More subjects reported AST or ALT elevations (greater than or equal to 3 times the upper limit of normal) when using pirfenidone in combination with nintedanib (n=3 (6%)) compared to nintedanib alone (n=0) [see Warnings and Precautions (5.2, 5.3)].

Chronic Fibrosing Interstitial Lung Diseases with a Progressive Phenotype

OFEV was studied in a phase 3, double-blind, placebo-controlled trial (Study 5) in which 663 patients with chronic fibrosing ILDs with a progressive phenotype were randomized to receive OFEV 150 mg twice daily (n=332) or placebo (n=331) for at least 52 weeks. At 52 weeks, the median duration of exposure was 12 months for patients in both treatment arms. Subjects ranged in age from 27 to 87 years (median age of 67 years). The majority of patients were Caucasian (74%) or Asian (25%). Most patients were male (54%).

The most frequent serious adverse event reported in patients treated with OFEV, more than placebo, was pneumonia (4% vs. 3%). Adverse events leading to death were reported in 3% of patients treated with OFEV and in 5% of patients treated with placebo. No pattern was identified in the adverse events leading to death.

Adverse reactions leading to permanent dose reductions were reported in 33% of OFEV-treated patients and 4% of placebo-treated patients. The most frequent adverse reaction that led to permanent dose reduction in the patients treated with OFEV was diarrhea (16%).

Adverse reactions leading to discontinuation were reported in 20% of OFEV-treated patients and 10% of placebo-treated patients. The most frequent adverse reaction that led to discontinuation in OFEV-treated patients was diarrhea (6%).

The safety profile in patients with chronic fibrosing ILDs with a progressive phenotype treated with OFEV was consistent with that observed in IPF patients. In addition, the following adverse events were reported in OFEV more than placebo in chronic progressive fibrosing ILD: nasopharyngitis (13% vs. 12%), upper respiratory tract infection (7% vs. 6%), urinary tract infection (6% vs. 4%), fatigue (10% vs. 6%), and back pain (6% vs. 5%).

Systemic Sclerosis-Associated Interstitial Lung Disease

OFEV was studied in a phase 3, randomized, double-blind, placebo-controlled trial (Study 4) in which 576 patients with SSc-ILD received OFEV 150 mg twice daily (n=288) or placebo (n=288). Patients were to receive treatment for at least 52 weeks; individual patients were treated for up to 100 weeks. The median duration of exposure was 15 months for patients treated with OFEV and 16 months for patients treated with placebo. Subjects ranged in age from 20 to 79 years (median age of 55 years). Most patients were female (75%). Patients were mostly Caucasian (67%), Asian (25%), or Black (6%). At baseline, 49% of patients were on stable therapy with mycophenolate.

The most frequent serious adverse events reported in patients treated with OFEV, more than placebo, were interstitial lung disease (2.4% nintedanib vs. 1.7% placebo) and pneumonia (2.8% nintedanib vs. 0.3% placebo). Within 52 weeks, 5 patients treated with OFEV (1.7%) and 4 patients treated with placebo (1.4%) died. There was no pattern among adverse events leading to death in either treatment arm.

Adverse reactions leading to permanent dose reductions were reported in 34% of OFEV-treated patients and 4% of placebo-treated patients. The most frequent adverse reaction that led to permanent dose reduction in the patients treated with OFEV was diarrhea (22%).

Adverse reactions leading to discontinuation were reported in 16% of OFEV-treated patients and 9% of placebo-treated patients. The most frequent adverse reactions that led to discontinuation in OFEV-treated patients were diarrhea (7%), nausea (2%), vomiting (1%), abdominal pain (1%), and interstitial lung disease (1%).

The safety profile in patients treated with OFEV with or without mycophenolate at baseline was comparable.

The most common adverse reactions with an incidence of greater than or equal to 5% in OFEV-treated patients and more commonly than in placebo are listed in Table 2.

Table 2 Adverse Reactions Occurring in ≥5% of OFEV-treated Patients with Systemic Sclerosis-Associated Interstitial Lung Disease and More Commonly Than Placebo in Study 4
Adverse Reaction | OFEV, 150 mg n=288 | Placebo n=288
Diarrhea | 76% | 32%
Nausea | 32% | 14%
Vomiting | 25% | 10%
Skin ulcer | 18% | 17%
Abdominal paina | 18% | 11%
Liver enzyme elevationb | 13% | 3%
Weight decreased | 12% | 4%
Fatigue | 11% | 7%
Decreased appetite | 9% | 4%
Headache | 9% | 8%
Pyrexia | 6% | 5%
Back pain | 6% | 4%
Dizziness | 6% | 4%
Hypertensionc | 5% | 2%
a Includes abdominal pain, abdominal pain upper, abdominal pain lower, and esophageal pain.
b Includes alanine aminotransferase increased, gamma-glutamyltransferase increased, aspartate aminotransferase increased, hepatic enzyme increased, blood alkaline phosphatase increased, transaminase increased, and hepatic function abnormal.
c Includes hypertension, blood pressure increased, and hypertensive crisis.

In addition, alopecia was reported in patients treated with OFEV, more than placebo (1.4% vs. 1.0%).

6.2 Postmarketing Experience

The following adverse reactions have been identified during postapproval use of OFEV. Because these reactions are reported voluntarily from a population of uncertain size, it is not always possible to reliably estimate their frequency or establish a causal relationship to drug exposure.

Blood and Lymphatic System Disorders: Thrombocytopenia
Gastrointestinal Disorders: Pancreatitis
Hepatobiliary Disorders: Drug-induced liver injury
Nervous System Disorders: Posterior reversible encephalopathy syndrome
Renal and Urinary Disorders: Proteinuria
Skin and Subcutaneous Tissue Disorders: Pruritus, rash
Vascular Disorders: Non-serious and serious bleeding events, some of which were fatal

7 DRUG INTERACTIONS

7.1 P-glycoprotein (P-gp) and CYP3A4 Inhibitors and Inducers

Nintedanib is a substrate of P-gp and, to a minor extent, CYP3A4 [see Clinical Pharmacology (12.3)]. Coadministration with oral doses of a P-gp and CYP3A4 inhibitor, ketoconazole, increased exposure to nintedanib by 60%. Concomitant use of P-gp and CYP3A4 inhibitors (e.g., erythromycin) with OFEV may increase exposure to nintedanib [see Clinical Pharmacology (12.3)]. In such cases, patients should be monitored closely for tolerability of OFEV. Management of adverse reactions may require interruption, dose reduction, or discontinuation of therapy with OFEV [see Dosage and Administration (2.4)].

Coadministration with oral doses of a P-gp and CYP3A4 inducer, rifampicin, decreased exposure to nintedanib by 50%. Concomitant use of P-gp and CYP3A4 inducers (e.g., carbamazepine, phenytoin, and St. John's wort) with OFEV should be avoided as these drugs may decrease exposure to nintedanib [see Clinical Pharmacology (12.3)].

7.2 Anticoagulants

Nintedanib is a VEGFR inhibitor and may increase the risk of bleeding. Monitor patients on full anticoagulation therapy closely for bleeding and adjust anticoagulation treatment as necessary [see Warnings and Precautions (5.6)].

7.3 Pirfenidone

In a multiple-dose study conducted to assess the pharmacokinetic effects of concomitant treatment with nintedanib and pirfenidone, the coadministration of nintedanib with pirfenidone did not alter the exposure of either agent [see Clinical Pharmacology (12.3)]. Therefore, no dose adjustment is necessary during concomitant administration of nintedanib with pirfenidone.

7.4 Bosentan

Coadministration of nintedanib with bosentan did not alter the pharmacokinetics of nintedanib [see Clinical Pharmacology (12.3)].

8 USE IN SPECIFIC POPULATIONS

8.1 Pregnancy

Risk Summary

Based on findings from animal studies and its mechanism of action [see Clinical Pharmacology (12.1)], OFEV can cause fetal harm when administered to a pregnant woman. There are no data on the use of OFEV during pregnancy. In animal studies of pregnant rats and rabbits treated during organogenesis, nintedanib caused embryo-fetal deaths and structural abnormalities at less than (rats) and approximately 5 times (rabbits) the maximum recommended human dose [see Data]. Advise pregnant women of the potential risk to a fetus.

The estimated background risk of major birth defects and miscarriage for the indicated population is unknown. In the U.S. general population, the estimated background risk of major birth defects is 2% to 4% and miscarriage in clinically recognized pregnancies is 15% to 20%.

Data

Animal Data

In animal reproduction toxicity studies, nintedanib caused embryo-fetal deaths and structural abnormalities in rats and rabbits at less than and approximately 5 times the maximum recommended human dose (MRHD) in adults (on a plasma AUC basis at maternal oral doses of 2.5 and 15 mg/kg/day in rats and rabbits, respectively). Malformations included abnormalities in the vasculature, urogenital, and skeletal systems. Vasculature anomalies included missing or additional major blood vessels. Skeletal anomalies included abnormalities in the thoracic, lumbar, and caudal vertebrae (e.g., hemivertebra, missing, or asymmetrically ossified), ribs (bifid or fused), and sternebrae (fused, split, or unilaterally ossified). In some fetuses, organs in the urogenital system were missing. In rabbits, a significant change in sex ratio was observed in fetuses (female:male ratio of approximately 71%:29%) at approximately 15 times the MRHD in adults (on an AUC basis at a maternal oral dose of 60 mg/kg/day). Nintedanib decreased post-natal viability of rat pups during the first 4 post-natal days when dams were exposed to less than the MRHD (on an AUC basis at a maternal oral dose of 10 mg/kg/day).

8.2 Lactation

Risk Summary

There is no information on the presence of nintedanib in human milk, the effects on the breast-fed infant or the effects on milk production. Nintedanib and/or its metabolites are present in the milk of lactating rats [see Data]. Because of the potential for serious adverse reactions in nursing infants from OFEV, advise women that breastfeeding is not recommended during treatment with OFEV.

Data

Milk and plasma of lactating rats have similar concentrations of nintedanib and its metabolites.

8.3 Females and Males of Reproductive Potential

Based on findings from animal studies and its mechanism of action, OFEV can cause fetal harm when administered to a pregnant woman and may reduce fertility in females of reproductive potential [see Use in Specific Populations (8.1), Clinical Pharmacology (12.1, 12.3), and Nonclinical Toxicology (13.1)]. Counsel patients on pregnancy prevention and planning.

Pregnancy Testing

Verify the pregnancy status of females of reproductive potential prior to treatment with OFEV and during treatment as appropriate [see Dosage and Administration (2.1), Warnings and Precautions (5.4), and Use in Specific Populations (8.1)].

Contraception

OFEV can cause fetal harm when administered to a pregnant woman. Advise females of reproductive potential to avoid becoming pregnant while receiving treatment with OFEV. Advise females of reproductive potential to use highly effective contraception at initiation of, during treatment, and for at least 3 months after taking the last dose of OFEV. Nintedanib does not change the exposure to oral contraceptive containing ethinylestradiol and levonorgestrel in patients with SSc-ILD. However, the efficacy of oral hormonal contraceptives may be compromised by vomiting and/or diarrhea or other conditions where the drug absorption may be reduced. Advise women taking oral hormonal contraceptives experiencing these conditions to use alternative highly effective contraception.

Infertility

Based on animal data, OFEV may reduce fertility in females of reproductive potential [see Nonclinical Toxicology (13.1)].

8.4 Pediatric Use

The safety and effectiveness of OFEV have not been established in pediatric patients for the treatment of fibrosing interstitial lung diseases. Effectiveness was not demonstrated in a randomized, double-blind, placebo-controlled study conducted in 26 OFEV-treated pediatric patients aged 6 to 17 years with fibrosing interstitial lung diseases, who were treated with OFEV based on weight.

Animal Toxicity Data

In repeat-dose toxicology studies, young animals (mice, rats, and monkeys) dosed with nintedanib showed changes in the bone and fast-growing teeth. Bone changes include thickening of the growth plate in all species. These changes were fully or at least partially reversible in rats and monkeys; reversibility in mice has not been studied.

Tooth changes include broken incisors and discoloration in rodents. These changes were irreversible after discontinuation of nintedanib treatment.

8.5 Geriatric Use

Of the total number of subjects in phase 2 and 3 clinical studies of OFEV in IPF (Study 1, Study 2, and Study 3), 61% were 65 and over, while 16% were 75 and over. In the chronic fibrosing ILDs with a progressive phenotype clinical study (Study 5), 61% were 65 and over, while 19% were 75 and older. In SSc-ILD (Study 4), 21.4% were 65 and over, while 1.9% were 75 and older. In phase 3 studies, no overall differences in effectiveness were observed between subjects who were 65 and over and younger subjects; no overall differences in safety were observed between subjects who were 65 and over or 75 and over and younger subjects, but greater sensitivity of some older individuals cannot be ruled out.

8.6 Hepatic Impairment

Nintedanib is predominantly eliminated via biliary/fecal excretion (greater than 90%). In a PK study performed in patients with hepatic impairment (Child Pugh A, Child Pugh B), exposure to nintedanib was increased [see Clinical Pharmacology (12.3)]. In patients with mild hepatic impairment (Child Pugh A), the recommended dosage of OFEV is 100 mg twice daily [see Dosage and Administration (2.3)]. Monitor for adverse reactions and consider treatment interruption, or discontinuation for management of adverse reactions in these patients [see Dosage and Administration (2.4)]. Treatment of patients with moderate (Child Pugh B) and severe (Child Pugh C) hepatic impairment with OFEV is not recommended [see Warnings and Precautions (5.1)].

8.7 Renal Impairment

Based on a single-dose study, less than 1% of the total dose of nintedanib is excreted via the kidney [see Clinical Pharmacology (12.3)]. Adjustment of the starting dose in patients with mild to moderate renal impairment is not required. The safety, efficacy, and pharmacokinetics of nintedanib have not been studied in patients with severe renal impairment (less than 30 mL/min CrCl) and end-stage renal disease.

8.8 Smokers

Smoking was associated with decreased exposure to OFEV [see Clinical Pharmacology (12.3)], which may alter the efficacy profile of OFEV. Encourage patients to stop smoking prior to treatment with OFEV and to avoid smoking when using OFEV.

10 OVERDOSAGE

In IPF trials, one patient was inadvertently exposed to a dose of 600 mg daily for a total of 21 days. A non-serious adverse event (nasopharyngitis) occurred and resolved during the period of incorrect dosing, with no onset of other reported events. Overdosage was also reported in two patients in oncology studies who were exposed to a maximum of 600 mg twice daily for up to 8 days. Adverse events reported were consistent with the existing safety profile of OFEV. Both patients recovered. In case of overdosage, interrupt treatment and initiate general supportive measures as appropriate.

11 DESCRIPTION

OFEV capsules contain nintedanib, a kinase inhibitor [see Mechanism of Action (12.1)]. Nintedanib is presented as the ethanesulfonate salt (esylate), with the chemical name 1H-Indole-6-carboxylic acid, 2,3-dihydro-3-[[[4-[methyl[(4-methyl-1-piperazinyl)acetyl]amino]phenyl]amino]phenylmethylene]-2-oxo-,methyl ester, (3Z)-, ethanesulfonate (1:1).

Its structural formula is:

Nintedanib esylate is a bright yellow powder with an empirical formula of C31H33N5O4∙C2H6O3S and a molecular weight of 649.76 g/mol.

OFEV capsules for oral administration are available in 2 dose strengths containing 100 mg or 150 mg of nintedanib (equivalent to 120.40 mg or 180.60 mg nintedanib ethanesulfonate, respectively). The inactive ingredients of OFEV are the following: Fill Material: hard fat, lecithin, triglycerides. Capsule Shell: ferric oxide red, ferric oxide yellow, gelatin, glycerol, titanium dioxide.

12 CLINICAL PHARMACOLOGY

12.1 Mechanism of Action

Nintedanib is a small molecule that inhibits multiple receptor tyrosine kinases (RTKs) and non-receptor tyrosine kinases (nRTKs). Nintedanib inhibits the following RTKs: platelet-derived growth factor receptor (PDGFR) α and β, fibroblast growth factor receptor (FGFR) 1-3, vascular endothelial growth factor receptor (VEGFR) 1-3, colony stimulating factor 1 receptor (CSF1R), and Fms-like tyrosine kinase-3 (FLT-3). These kinases except for FLT-3 have been implicated in pathogenesis of interstitial lung diseases (ILD). Nintedanib binds competitively to the adenosine triphosphate (ATP) binding pocket of these kinases and blocks the intracellular signaling cascades, which have been demonstrated to be involved in the pathogenesis of fibrotic tissue remodeling in ILD. Nintedanib also inhibits the following nRTKs: Lck, Lyn and Src kinases. The contribution of FLT-3 and nRTK inhibition to nintedanib efficacy in ILD is unknown.

12.2 Pharmacodynamics

Cardiac Electrophysiology

In a study in renal cell cancer patients, QT/QTc measurements were recorded and showed that a single oral dose of 200 mg nintedanib as well as multiple oral doses of 200 mg nintedanib administered twice daily for 15 days did not prolong the QTcF interval.

12.3 Pharmacokinetics

The PK properties of nintedanib were similar in healthy volunteers, patients with IPF, patients with chronic fibrosing ILDs with a progressive phenotype, patients with SSc-ILD, and cancer patients. The PK of nintedanib is linear. Dose proportionality was shown by an increase of nintedanib exposure with increasing doses (dose range 50 to 450 mg once daily and 150 to 300 mg twice daily). Accumulation upon multiple administrations in patients with IPF was 1.76-fold for AUC. Steady-state plasma concentrations were achieved within one week of dosing. Nintedanib trough concentrations remained stable for more than one year. The inter-individual variability in the PK of nintedanib was moderate to high (coefficient of variation of standard PK parameters in the range of 30% to 70%), intra-individual variability low to moderate (coefficients of variation below 40%).

Absorption

Nintedanib reached maximum plasma concentrations approximately 2 to 4 hours after oral administration as a soft gelatin capsule under fed conditions. The absolute bioavailability of a 100 mg dose was 4.7% (90% CI: 3.62 to 6.08) in healthy volunteers. Absorption and bioavailability are decreased by transporter effects and substantial first-pass metabolism.

After food intake, nintedanib exposure increased by approximately 20% compared to administration under fasted conditions (90% CI: 95.3% to 152.5%) and absorption was delayed (median tmax fasted: 2.00 hours; fed: 3.98 hours), irrespective of the food type.

Distribution

Nintedanib follows bi-phasic disposition kinetics. After intravenous infusion, a high volume of distribution which was larger than total body volume (Vss: 1050 L) was observed.

The in vitro protein binding of nintedanib in human plasma was high, with a bound fraction of 97.8%. Serum albumin is considered to be the major binding protein. Nintedanib is preferentially distributed in plasma with a blood to plasma ratio of 0.87.

Elimination

The effective half-life of nintedanib in patients with IPF was 9.5 hours (gCV 31.9%). Total plasma clearance after intravenous infusion was high (CL: 1390 mL/min; gCV 28.8%). Urinary excretion of unchanged drug within 48 hours was about 0.05% of the dose after oral and about 1.4% of the dose after intravenous administration; the renal clearance was 20 mL/min.

Metabolism

The prevalent metabolic reaction for nintedanib is hydrolytic cleavage by esterases resulting in the free acid moiety BIBF 1202. BIBF 1202 is subsequently glucuronidated by UGT enzymes, namely UGT 1A1, UGT 1A7, UGT 1A8, and UGT 1A10 to BIBF 1202 glucuronide. Only a minor extent of the biotransformation of nintedanib consisted of CYP pathways, with CYP3A4 being the predominant enzyme involved. The major CYP-dependent metabolite could not be detected in plasma in the human absorption, distribution, metabolism, and elimination study. In vitro, CYP-dependent metabolism accounted for about 5% compared to about 25% ester cleavage.

Excretion

The major route of elimination of drug-related radioactivity after oral administration of [^14C] nintedanib was via fecal/biliary excretion (93.4% of dose), and the majority of OFEV was excreted as BIBF 1202. The contribution of renal excretion to the total clearance was low (0.65% of dose). The overall recovery was considered complete (above 90%) within 4 days after dosing.

Specific Populations

Age, Body Weight, and Sex

Based on population PK analysis, age and body weight were correlated with nintedanib exposure. However, the effects on exposure are not sufficient to warrant a dose adjustment. There was no influence of sex on the exposure of nintedanib.

Patients with Renal Impairment

Based on a population PK analysis of data from 933 patients with IPF, exposure to nintedanib was not influenced by mild (CrCl: 60 to 90 mL/min; n=399) or moderate (CrCl: 30 to 60 mL/min; n=116) renal impairment. Data in severe renal impairment (CrCl below 30 mL/min) was limited.

Patients with Hepatic Impairment

A dedicated single-dose phase I pharmacokinetics study of OFEV compared 8 subjects with mild hepatic impairment (Child Pugh A) and 8 subjects with moderate hepatic impairment (Child Pugh B) to 17 subjects with normal hepatic function. In subjects with mild hepatic impairment, the mean exposure to nintedanib was 2.4-fold higher based on Cmax (90% CI: 1.6 to 3.6) and 2.2-fold higher based on AUC0-inf (90% CI: 1.4 to 3.5). In subjects with moderate hepatic impairment, exposure was 6.9-fold higher based on Cmax (90% CI: 4.4 to 11.0) and 7.6-fold higher based on AUC0-inf (90% CI: 5.1 to 11.3). Subjects with severe hepatic impairment (Child Pugh C) have not been studied.

Smokers

In the population PK analysis, the exposure of nintedanib was 21% lower in current smokers compared to ex- and never-smokers. The effect is not sufficient to warrant a dose adjustment.

Drug Interaction Studies

Potential for Nintedanib to Affect Other Drugs

Effect of nintedanib coadministration on pirfenidone AUC and Cmax was evaluated in a multiple-dose study. Nintedanib did not have an effect on the exposure of pirfenidone.

Fifteen female patients with SSc-ILD received a single dose of a combination of 30 mcg ethinylestradiol and 150 mcg levonorgestrel before and after twice daily dosing of 150 mg nintedanib for at least 10 days. Co-administration of nintedanib did not change the exposure of ethinylestradiol and levonorgestrel [see Warnings and Precautions (5.4) and Use in Specific Populations (8.3)].

In in vitro studies, nintedanib was shown not to be an inhibitor of OATP-1B1, OATP-1B3, OATP-2B1, OCT-2, or MRP-2. In vitro studies also showed that nintedanib has weak inhibitory potential on OCT-1, BCRP, and P-gp; these findings are considered to be of low clinical relevance. Nintedanib and its metabolites, BIBF 1202 and BIBF 1202 glucuronide, did not inhibit or induce CYP enzymes in vitro.

Potential for Other Drugs to Affect Nintedanib

Nintedanib is a substrate of P-gp and, to a minor extent, CYP3A4. Coadministration with the P-gp and CYP3A4 inhibitor, ketoconazole, increased exposure to nintedanib 1.61-fold based on AUC and 1.83-fold based on Cmax in a dedicated drug-drug interaction study. In a drug-drug interaction study with the P-gp and CYP3A4 inducer, rifampicin, exposure to nintedanib decreased to 50.3% based on AUC and to 60.3% based on Cmax upon coadministration with rifampicin compared to administration of nintedanib alone.

Effect of pirfenidone coadministration on nintedanib AUC and Cmax was evaluated in a multiple-dose drug-drug interaction study. Pirfenidone did not have an effect on the exposure of nintedanib. Concomitant treatment with nintedanib and pirfenidone was also investigated in a separate trial, which was an exploratory open-label, randomized (1:1) trial of nintedanib 150 mg twice daily with add-on pirfenidone (titrated to 801 mg three times a day) compared to nintedanib 150 mg twice daily alone in 105 randomized patients for 12 weeks. Similar nintedanib trough plasma concentrations were observed when comparing patients receiving nintedanib alone with patients receiving nintedanib with add-on pirfenidone.

Healthy volunteers received a single dose of 150 mg nintedanib before and after multiple dosing of 125 mg bosentan twice daily at steady state. Coadministration of nintedanib with bosentan did not alter the pharmacokinetics of nintedanib.

Nintedanib displays a pH-dependent solubility profile with increased solubility at acidic pH less than 3. However, in the clinical trials, coadministration with proton pump inhibitors or histamine H2 antagonists did not influence the exposure (trough concentrations) of nintedanib.

In in vitro studies, nintedanib was shown not to be a substrate of OATP-1B1, OATP-1B3, OATP-2B1, OCT-2, MRP-2, or BCRP. In vitro studies also showed that nintedanib was a substrate of OCT-1; these findings are considered to be of low clinical relevance.

13 NONCLINICAL TOXICOLOGY

13.1 Carcinogenesis, Mutagenesis, Impairment of Fertility

Two-year oral carcinogenicity studies of nintedanib in rats and mice have not revealed any evidence of carcinogenic potential. Nintedanib was dosed up to 10 and 30 mg/kg/day in rats and mice, respectively. These doses were less than and approximately 4 times the MRHD on a plasma drug AUC basis.

Nintedanib was negative for genotoxicity in the in vitro bacterial reverse mutation assay, the mouse lymphoma cell forward mutation assay, and the in vivo rat micronucleus assay.

In rats, nintedanib reduced female fertility at exposure levels approximately 3 times the MRHD (on an AUC basis at an oral dose of 100 mg/kg/day). Effects included increases in resorption and post-implantation loss, and a decrease in gestation index. Changes in the number and size of corpora lutea in the ovaries were observed in chronic toxicity studies in rats and mice. An increase in the number of females with resorptions only was observed at exposures approximately equal to the MRHD (on an AUC basis at an oral dose of 20 mg/kg/day). Nintedanib had no effects on male fertility in rats at exposure levels approximately 3 times the MRHD (on an AUC basis at an oral dose of 100 mg/kg/day).

14 CLINICAL STUDIES

14.1 Idiopathic Pulmonary Fibrosis

The clinical efficacy of OFEV has been studied in 1231 patients with IPF in one phase 2 (Study 1 [NCT00514683]) and two phase 3 studies (Study 2 [NCT01335464] and Study 3 [NCT01335477]). These were randomized, double-blind, placebo-controlled studies comparing treatment with OFEV 150 mg twice daily to placebo for 52 weeks.

Study 2 and Study 3 were identical in design. Study 1 was very similar in design. Patients were randomized in a 3:2 ratio (1:1 for Study 1) to either OFEV 150 mg or placebo twice daily for 52 weeks. Study 1 also included other treatment arms (50 mg daily, 50 mg twice daily, and 100 mg twice daily) that are not further discussed. The primary endpoint was the annual rate of decline in Forced Vital Capacity (FVC). Time to first acute IPF exacerbation was a key secondary endpoint in Study 2 and Study 3 and a secondary endpoint in Study 1. Change from baseline in FVC percent predicted and survival were additional secondary endpoints in all studies.

Patients were required to have a diagnosis of IPF (ATS/ERS/JRS/ALAT criteria) for less than 5 years. Diagnoses were centrally adjudicated based on radiologic and, if applicable, histopathologic confirmation. Patients were required to be greater than or equal to 40 years of age with an FVC greater than or equal to 50% of predicted and a carbon monoxide diffusing capacity (DLCO, corrected for hemoglobin) 30% to 79% of predicted. Patients with relevant airways obstruction (i.e., pre-bronchodilator FEV1/FVC less than 0.7) or, in the opinion of the investigator, likely to receive a lung transplant during the studies were excluded (being listed for lung transplant was acceptable for inclusion). Patients with greater than 1.5 times ULN of ALT, AST, or bilirubin, patients with a known risk or predisposition to bleeding, patients receiving a full dose of anticoagulation treatment, and patients with a recent history of myocardial infarction or stroke were excluded from the studies. Patients were also excluded if they received other investigational therapy, azathioprine, cyclophosphamide, or cyclosporine A within 8 weeks of entry into this trial, or n-acetyl cysteine and prednisone (greater than 15 mg/day or equivalent) within 2 weeks. The majority of patients were Caucasian (60%) or Asian (30%) and male (79%). Patients had a mean age of 67 years and a mean FVC percent predicted of 80%.

Annual Rate of Decline in FVC

A statistically significant reduction in the annual rate of decline of FVC (in mL) was demonstrated in patients receiving OFEV compared to patients receiving placebo based on the random coefficient regression model, adjusted for gender, height, and age. The treatment effect on FVC was consistent in all 3 studies. See Table 3 for individual study results.

Table 3 Annual Rate of Decline in FVC (mL) in Study 1, Study 2, and Study 3a
 | Study 1 |  | Study 2 |  | Study 3
 | OFEV 150 mg twice daily | Placebo | OFEV 150 mg twice daily | Placebo | OFEV 150 mg twice daily | Placebo
Number of analyzed patients | 84 | 83 | 309 | 204 | 329 | 219
Ratea of decline over 52 weeks | -60 | -191 | -115 | -240 | -114 | -207
Comparison vs placebo
Differenceb | 131 |  | 125 |  | 94
95% CI | (27, 235) |  | (78, 173) |  | (45, 143)
aRandomized set in Study 1; treated set in Study 2 and Study 3
bEstimated based on a random coefficient regression model

Figure 1 displays the change from baseline over time in both treatment groups for Study 2. When the mean observed FVC change from baseline was plotted over time, the curves diverged at all timepoints through Week 52. Similar plots were seen for Study 1 and Study 3.

Figure 1 Mean (SEM) Observed FVC Change from Baseline (mL) Over Time in Study 2

bid = twice daily

Change from Baseline in Percent Predicted Forced Vital Capacity

Figure 2 presents the cumulative distribution for all cut-offs for the change from baseline in FVC percent predicted at Week 52 for Study 2. For all categorical declines in lung function, the proportion of patients declining was lower on OFEV than on placebo. Study 3 showed similar results.

Figure 2 Cumulative Distribution of Patients by Change in Percent Predicted FVC from Baseline to Week 52 (Study 2). [Missing data for change from baseline at Week 52 in percent predicted FVC (due to death, lost to follow-up or censoring before 52 weeks) was imputed using the worst decline from baseline at Week 52 observed among all patients with available data, regardless of treatment. bid = twice daily] The vertical lines indicate ≥0% decline or ≥10% decline.

Time to First Acute IPF Exacerbation

Acute IPF exacerbation was defined as unexplained worsening or development of dyspnea within 30 days, new diffuse pulmonary infiltrates on chest x-ray, and/or new high-resolution CT parenchymal abnormalities with no pneumothorax or pleural effusion, and exclusion of alternative causes. Acute IPF exacerbation was adjudicated in Study 2 and Study 3. In Study 1 (investigator-reported) and Study 3 (adjudicated), the risk of first acute IPF exacerbation over 52 weeks was significantly reduced in patients receiving OFEV compared to placebo (hazard ratio [HR]: 0.16, 95% CI: 0.04, 0.71) and (HR: 0.20, 95% CI: 0.07, 0.56), respectively. In Study 2 (adjudicated), there was no difference between the treatment groups (HR: 0.55, 95% CI: 0.20, 1.54).

Survival

Survival was evaluated for OFEV compared to placebo in Study 2 and Study 3 as an exploratory analysis to support the primary endpoint (FVC). All-cause mortality was assessed over the study duration and available follow-up period, irrespective of cause of death and whether patients continued treatment. All-cause mortality did not show a statistically significant difference (See Figure 3).

Figure 3 Kaplan-Meier Estimates of All-Cause Mortality at Vital Status – End of Study: Study 2 and Study 3

bid = twice daily

14.2 Chronic Fibrosing Interstitial Lung Diseases with a Progressive Phenotype

The clinical efficacy of OFEV has been studied in patients with chronic fibrosing ILDs with a progressive phenotype in a randomized, double-blind, placebo-controlled phase 3 trial (Study 5 [NCT02999178]). A total of 663 patients were randomized in a 1:1 ratio to receive either OFEV 150 mg twice daily or matching placebo for at least 52 weeks. Randomization was stratified based on high resolution computed tomography (HRCT) fibrotic pattern as assessed by central readers: 412 patients with UIP-like HRCT pattern and 251 patients with other HRCT fibrotic patterns were randomized. There were 2 co-primary populations defined for the analyses in this trial: all patients (the overall population) and patients with HRCT with UIP-like HRCT fibrotic pattern.

The primary endpoint was the annual rate of decline in FVC (in mL) over 52 weeks. Other endpoints included time to first acute ILD exacerbation and time to death.

Patients with a clinical diagnosis of a chronic fibrosing ILD were selected if they had relevant fibrosis (greater than 10% fibrotic features) on HRCT and presented with clinical signs of progression (defined as FVC decline ≥10%, FVC decline ≥5% and <10% with worsening symptoms or imaging, or worsening symptoms and worsening imaging all in the 24 months prior to screening). Patients were required to have an FVC greater than or equal to 45% of predicted and a DLCO 30% to less than 80% of predicted. Patients were required to have progressed despite management deemed appropriate in clinical practice by investigators for the patient's relevant ILD.

Patients with IPF, relevant airways obstruction (i.e., pre-bronchodilator FEV1/FVC less than 0.7), or significant pulmonary hypertension were excluded from the trial. Patients with greater than 1.5 times ULN of ALT, AST, or bilirubin, patients with a known risk or predisposition to bleeding, patients receiving a full dose of anticoagulation treatment, and patients with a recent history of myocardial infarction or stroke were excluded. Patients were also excluded if they received other investigational therapy, azathioprine, cyclosporine, mycophenolate mofetil, tacrolimus, oral corticosteroids greater than 20 mg/day, or the combination of oral corticosteroids + azathioprine + n-acetylcysteine within 4 weeks of randomization, cyclophosphamide within 8 weeks prior to randomization, rituximab within 6 months, or previous treatment with nintedanib or pirfenidone.

The majority of patients were Caucasian (74%) or Asian (25%). Patients were mostly male (54%) and had a mean age of 66 years and a mean FVC percent predicted of 69%, and 49% were never-smokers. The underlying clinical ILD diagnoses in groups represented in the trial were hypersensitivity pneumonitis (26%), autoimmune ILDs (26%), idiopathic nonspecific interstitial pneumonia (19%), unclassifiable idiopathic interstitial pneumonia (17%), and other ILDs (12%).

Annual Rate of Decline in FVC

There was a statistically significant reduction in the annual rate of decline in FVC (in mL) over 52 weeks in patients receiving OFEV compared to patients receiving placebo. The annual rate of decline in FVC (in mL) over 52 weeks was significantly reduced by 107 mL in patients receiving OFEV compared to patients receiving placebo. Results in the subpopulations of patients with HRCT with UIP-like fibrotic pattern and patients with other fibrotic patterns (Other HRCT) are included with the overall population in Table 4.

Table 4 Annual Rate of Decline in FVC (mL) in Study 5
 | Overall |  | UIP-like Subpopulation |  | Other HRCT Subpopulation
 | OFEV | Placebo | OFEV | Placebo | OFEV | Placebo
Number of analyzed patients | 331 | 331 | 206 | 206 | 125 | 125
Adjusted annual rate of decline over 52 weeks | -81 | -188 | -83 | -211 | -79 | -154
Comparison vs placebo differencea | 107 |  | 128 |  | 75*
95% CI | (65, 148) |  | (71, 186) |  | (16, 135)*
*Comparison based on the Other HRCT subpopulation was not included in the multiple testing procedure. Values shown here are for descriptive purposes.
aBased on a random coefficient regression model with fixed categorical effects of treatment, HRCT pattern, fixed continuous effects of time, baseline FVC (mL), and including treatment by time and baseline by time interactions

A post-hoc exploratory analysis by ILD diagnosis was performed and is shown in Figure 4. Treatment response across ILD diagnoses was consistent for FVC.

Figure 4 Annual Rate of Decline in FVC (mL) over 52 Weeks based on Underlying ILD Diagnosis in Study 5*

ILD = interstitial lung disease; Autoimmune ILDs: includes rheumatoid arthritis-associated ILD, mixed connective tissue disease, systemic sclerosis-associated ILD, and other terms; Other ILDs: includes fibrosing ILDs not categorized under autoimmune ILDs, hypersensitivity pneumonitis, idiopathic nonspecific interstitial pneumonia, or unclassifiable idiopathic interstitial pneumonia. The three most common ILDs in this category are exposure-related ILD, sarcoidosis, and pleuro-parenchymal fibroelastosis.
*These results are from a post-hoc exploratory analysis. Values shown here are for descriptive purposes.

Figure 5 shows the change in FVC from baseline over time in the treatment groups. When the mean observed FVC change from baseline was plotted over time, the curves diverged at all timepoints through Week 52.

Figure 5 Mean (SEM) Observed FVC Change from Baseline (mL) Over 52 Weeks in Study 5

bid = twice daily

Percent Change from Baseline in Forced Vital Capacity

Figure 6 presents the percent change from baseline in FVC in mL at Week 52 for Study 5. For the majority of patients, the decline in lung function was less on OFEV than on placebo.

Figure 6 Histogram of the Percent Change in FVC (mL) from Baseline to Week 52 According to Treatment and Percent Increments or Decrements of 5 (Study 5)a

a Patients classified as having missing FVC data at Week 52 are those with no FVC assessment between Day 310 and Day 373.
bid = twice daily

Time to First Acute ILD Exacerbation

Acute ILD exacerbation was defined as unexplained worsening or development of dyspnea within 30 days, new diffuse pulmonary infiltrates on chest x-ray, and/or new HRCT parenchymal abnormalities with no pneumothorax or pleural effusion, and exclusion of alternative causes. Acute ILD exacerbations were not adjudicated.

The risk of first acute ILD exacerbation did not show a statistically significant difference between the OFEV group compared to placebo (52 week treatment period: HR 0.72, (95% CI: 0.38, 1.37); whole trial: HR 0.63 (95% CI: 0.37, 1.07)).

Survival

Survival was evaluated for OFEV compared to placebo in Study 5 to support the primary endpoint (FVC). All-cause mortality was assessed over the study duration and available follow-up period, irrespective of cause of death and whether patients continued treatment. All-cause mortality did not show a statistically significant difference (52 week treatment period: HR 0.94 (95% CI: 0.47, 1.86); whole trial: HR 0.78 (95% CI: 0.50, 1.21)).

14.3 Systemic Sclerosis-Associated Interstitial Lung Disease

The clinical efficacy of nintedanib has been studied in patients with SSc-ILD in a randomized, double-blind, placebo-controlled phase 3 trial (Study 4 [NCT02597933]). A total of 580 patients were randomized in a 1:1 ratio to receive either OFEV 150 mg twice daily or matching placebo for at least 52 weeks, of which 576 patients were treated. Randomization was stratified by anti-topoisomerase antibody (ATA) status. Individual patients remained on blinded trial treatment for up to 100 weeks. The primary endpoint was the annual rate of decline in FVC over 52 weeks. The absolute change from baseline in the modified Rodnan skin score (mRSS) at Week 52 was a key secondary endpoint. Mortality over the whole trial was an additional secondary endpoint.

Patients were diagnosed with SSc-ILD based upon the 2013 American College of Rheumatology / European League Against Rheumatism classification criteria for SSc with onset of disease (first non-Raynaud symptom) of less than 7 years and greater than or equal to 10% fibrosis on a chest high resolution computed tomography (HRCT) scan conducted within the previous 12 months. Patients were required to have an FVC greater than or equal to 40% of predicted and a DLCO 30-89% of predicted. Patients with relevant airways obstruction (i.e., pre-bronchodilator FEV1/FVC less than 0.7) or previous or planned hematopoietic stem cell transplant were excluded from the trial. Patients with greater than 1.5 times ULN of ALT, AST, or bilirubin, patients with a known risk or predisposition to bleeding, patients receiving a full dose of anticoagulation treatment, and patients with a recent history of myocardial infarction or stroke were excluded from the study. Patients were excluded if they had significant pulmonary hypertension, more than three digital fingertip ulcers, a history of severe digital necrosis requiring hospitalization, or a history of scleroderma renal crisis. Patients were also excluded if they received other investigational therapy, azathioprine within 8 weeks prior to randomization, cyclophosphamide or cyclosporine A within 6 months prior to randomization, or previous treatment with nintedanib or pirfenidone.

The majority of patients were female (75%). Patients were mostly Caucasian (67%), Asian (25%), or Black (6%). The mean age was 54 years. Overall, 52% of patients had diffuse cutaneous systemic sclerosis (SSc) and 48% had limited cutaneous SSc. The mean time since first onset of a non-Raynaud symptom was 3.49 years. At baseline, 49% of patients were on stable therapy with mycophenolate.

Annual Rate of Decline in FVC

The annual rate of decline of FVC (in mL) over 52 weeks was significantly reduced by 41 mL in patients receiving OFEV compared to patients receiving placebo, corresponding to a relative treatment effect of 44%. See Table 5.

Table 5 Annual Rate of Decline in FVC (mL) in Study 4
 | OFEV 150 mg twice daily | Placebo
Number of analyzed patients | 287 | 288
Adjusted rate of decline over 52 weeks | -52 | -93
Comparison vs placebo
Differencea | 41
95% CI | (3, 79)
aBased on a random coefficient regression model, adjusted for gender, height, age, ATA status, FVC at baseline, FVC at baseline-by-time

Figure 7 displays the change from baseline over time in both treatment groups. When the mean observed FVC change from baseline was plotted over time, the curves diverged at all timepoints through Week 52. Separation of the mean values is seen after 12 weeks of treatment.

Figure 7 Mean (SEM) Observed FVC Change from Baseline (mL) Over Time in Study 4

bid = twice daily

In two pre-specified subgroup efficacy analyses, the mean treatment difference in FVC decline at 52 weeks in patients were examined by region and mycophenolate use (Figure 8).

Figure 8 Subgroup Analyses of the Mean Treatment Difference in FVC (mL) Decline at Week 52 by Region and Mycophenolate Use (Study 4)

Percent Change from Baseline in Forced Vital Capacity

Figure 9 presents the percent change from baseline in FVC in mL at Week 52 for Study 4. For the majority of patients, the decline in lung function was less on OFEV than on placebo.

Figure 9 Histogram of the Percent Change in FVC (mL) from Baseline to Week 52 According to Treatment and Percent Increments or Decrements of 5 (Study 4)a

a Patients classified as having missing FVC data at Week 52 are those with no FVC assessment between Day 310 and Day 373.
bid = twice daily

Modified Rodnan Skin Score

No benefit in mRSS was observed in patients receiving OFEV. The adjusted mean absolute change from baseline in mRSS at Week 52 was comparable between the OFEV group (-2.17 (95% CI: -2.69, -1.65)) and the placebo group (-1.96 (95% CI: -2.48, -1.45)). The adjusted mean difference between the treatment groups was -0.21 (95% CI: -0.94, 0.53).

Survival

No difference in survival was observed in an exploratory analysis of mortality over the whole trial (OFEV: n=10 (3.5%) vs. placebo: n=9 (3.1%)). The analysis of time to death over the whole trial resulted in a HR of 1.16 (95% CI: 0.47, 2.84).

16 HOW SUPPLIED/STORAGE AND HANDLING

150 mg: brown, opaque, oblong, soft capsules marked in dark gray with the Boehringer Ingelheim company symbol and "150". They are packaged in HDPE bottles with a child-resistant closure, available as follows:

Bottles of 60 | NDC: 0597-0145-60

100 mg: peach, opaque, oblong, soft capsules marked in dark gray with the Boehringer Ingelheim company symbol and "100". They are packaged in HDPE bottles with a child-resistant closure, available as follows:

Bottles of 60 | NDC: 0597-0143-60

Storage

Store at 20°C to 25°C (68°F to 77°F); excursions permitted to 15°C to 30°C (59°F to 86°F) [see USP Controlled Room Temperature]. Protect from exposure to high humidity and avoid excessive heat. If repackaged, use USP tight container.

17 PATIENT COUNSELING INFORMATION

Advise the patient to read the FDA-approved patient labeling (Patient Information).

Elevated Liver Enzymes and Drug-Induced Liver Injury

Advise patients that they will need to undergo liver function testing periodically. Advise patients to immediately report any symptoms of a liver problem (e.g., skin or the whites of eyes turn yellow, urine turns dark or brown (tea colored), pain on the right side of stomach, bleed or bruise more easily than normal, lethargy, loss of appetite) [see Warnings and Precautions (5.2)].

Gastrointestinal Disorders

Inform patients that gastrointestinal disorders such as diarrhea, nausea, and vomiting were the most commonly reported gastrointestinal events occurring in patients who received OFEV. Advise patients that their healthcare provider may recommend hydration, antidiarrheal medications (e.g., loperamide), or anti-emetic medications to treat these side effects. Temporary dosage reductions or discontinuations may be required. Instruct patients to contact their healthcare provider at the first signs of diarrhea or for any severe or persistent diarrhea, nausea, or vomiting [see Warnings and Precautions (5.3) and Adverse Reactions (6.1)].

Embryo-Fetal Toxicity

Counsel patients on pregnancy prevention and planning. Advise females of reproductive potential of the potential risk to a fetus and to avoid becoming pregnant while receiving treatment with OFEV. Advise females of reproductive potential to use highly effective contraception at initiation of, during treatment, and for at least 3 months after taking the last dose of OFEV. Advise women taking oral hormonal contraceptives who experience vomiting and/or diarrhea or other conditions where the drug absorption may be reduced to contact their doctor to discuss alternative highly effective contraception. Advise female patients to notify their doctor if they become pregnant or suspect they are pregnant during therapy with OFEV [see Warnings and Precautions (5.4) and Use in Specific Populations (8.1, 8.3)].

Arterial Thromboembolic Events

Advise patients about the signs and symptoms of acute myocardial ischemia and other arterial thromboembolic events and the urgency to seek immediate medical care for these conditions [see Warnings and Precautions (5.5)].

Risk of Bleeding

Bleeding events have been reported. Advise patients to report unusual bleeding [see Warnings and Precautions (5.6)].

Gastrointestinal Perforation

Serious gastrointestinal perforation events have been reported. Advise patients to report signs and symptoms of gastrointestinal perforation [see Warnings and Precautions (5.7)].

Nephrotic Range Proteinuria

Nephrotic range proteinuria has been reported. Advise patients to report signs and symptoms of proteinuria (e.g., fluid retention, foamy urine) [see Warnings and Precautions (5.8)].

Lactation

Advise patients that breastfeeding is not recommended while taking OFEV [see Use in Specific Populations (8.2)].

Smokers

Encourage patients to stop smoking prior to treatment with OFEV and to avoid smoking when using OFEV [see Clinical Pharmacology (12.3)].

Administration

Instruct patients to take OFEV with food, to swallow OFEV capsules whole with liquid, and not to chew the capsules due to the bitter taste. Advise patients or caregivers not to open or crush OFEV capsules and to wash hands immediately and thoroughly if contact with the content of the capsule occurs. Advise patients to not make up for a missed dose [see Dosage and Administration (2.2)].

Distributed by:
Boehringer Ingelheim Pharmaceuticals, Inc.
Ridgefield, CT 06877 USA

Licensed from:
Boehringer Ingelheim International GmbH

OFEV is a registered trademark of and used under license from Boehringer Ingelheim International GmbH.

Copyright © 2025 Boehringer Ingelheim International GmbH
ALL RIGHTS RESERVED

COL13994BJ182024
SPL9116I

Patient Information
OFEV® (OH-fev)
(nintedanib capsules)

What is the most important information I should know about OFEV?

- OFEV can cause birth defects or death to an unborn baby. Women should not become pregnant while taking OFEV. Women who are able to become pregnant should have a pregnancy test before starting treatment with OFEV.
- Women who are able to become pregnant should use highly effective birth control at the start of treatment, during treatment, and for at least 3 months after treatment. Talk with your doctor about what birth control method is right for you during this time.
- Birth control pills may not work as well in women having vomiting, diarrhea, or other problems reducing the drug absorption. If you have any of these problems, talk with your doctor about which highly effective birth control method is right for you.
- If you become pregnant or think you are pregnant while taking OFEV, tell your doctor right away.

What is OFEV?

- OFEV is a prescription medicine used:
  - to treat adults with a lung disease called idiopathic pulmonary fibrosis (IPF).
  - to treat adults with a long-lasting (chronic) interstitial lung disease in which lung fibrosis continues to worsen (progress).
  - to slow the rate of decline in lung function in adults with systemic sclerosis-associated interstitial lung disease (SSc-ILD) (also known as scleroderma-associated ILD).
- It is not known if OFEV is safe and effective in children.

What should I tell my doctor before taking OFEV?
Before you take OFEV, tell your doctor about all of your medical conditions, including if you:

- have liver problems.
- have heart problems.
- have a history of blood clots.
- have a bleeding problem or a family history of a bleeding problem.
- have had recent surgery in your stomach (abdominal) area.
- are a smoker.
- are pregnant or plan to become pregnant. OFEV can harm your unborn baby. OFEV can cause birth defects or death to an unborn baby. See "What is the most important information I should know about OFEV?"
- are breastfeeding or plan to breastfeed. It is not known if OFEV passes into your breast milk. You should not breastfeed while taking OFEV.

Tell your doctor about all the medicines you take, including prescription and over-the-counter medicines, vitamins, and herbal supplements such as St. John's wort. Keep a list of the medicines you take and show it to your doctor and pharmacist when you get a new medicine.

How should I take OFEV?

- Take OFEV exactly as your doctor tells you to take it.
- Your doctor will tell you how much OFEV to take and when to take it.
- Take OFEV with food. Swallow the OFEV capsules whole with a liquid.
- Do not chew, crush, or open OFEV capsules. If you or your caregiver accidently comes in contact with the content of the capsule, wash hands well right away.
- If you miss a dose of OFEV, take your next dose at your regular time. Do not take the missed dose.
- Do not take more than 300 mg of OFEV in 1 day.
- If you take too much OFEV, call your doctor or go to the nearest hospital emergency room right away.
- Your doctor should do certain blood tests before you start taking OFEV.

What are the possible side effects of OFEV?
OFEV may cause serious side effects, including:

- See "What is the most important information I should know about OFEV?"
- liver problems. Call your doctor right away if you have unexplained symptoms such as yellowing of your skin or the white part of your eyes (jaundice), dark or brown (tea colored) urine, pain on the upper right side of your stomach area (abdomen), bleeding or bruising more easily than normal, feeling tired, or loss of appetite. Your doctor will do blood tests to check how well your liver is working before starting and during your treatment with OFEV.
- diarrhea, nausea, and vomiting. While you are taking OFEV, your doctor may recommend that you drink fluids or take medicine to treat these side effects. Tell your doctor if you have diarrhea, nausea, or vomiting or if these symptoms do not go away or become worse. Tell your doctor if you are taking over-the-counter laxatives, stool softeners, and other medicines or dietary supplements that can cause diarrhea.
- heart attack. Tell your doctor right away if you have symptoms of a heart problem. These symptoms may include chest pain or pressure, pain in your arms, back, neck or jaw, or shortness of breath.
- stroke. Tell your doctor right away if you have symptoms of a stroke. These symptoms may include numbness or weakness on 1 side of your body, trouble talking, headache, or dizziness.
- bleeding problems. OFEV may increase your chances of having bleeding problems. Tell your doctor if you have unusual bleeding, bruising, or wounds that do not heal. Tell your doctor if you are taking a blood thinner, including prescription blood thinners and over-the-counter aspirin.
- tear in your stomach or intestinal wall (perforation). OFEV may increase your chances of having a tear in your stomach or intestinal wall. Tell your doctor if you have pain or swelling in your stomach area.
- increased protein in your urine (proteinuria). OFEV may increase your chances of having protein in your urine. Tell your doctor if you have any signs and symptoms of protein in the urine such as foamy urine, swelling, including in your hands, arms, legs, or feet, or sudden weight gain.

The most common side effects of OFEV are diarrhea, nausea, stomach pain, vomiting, liver problems, decreased appetite, headache, weight loss, and high blood pressure.
These are not all the possible side effects of OFEV. For more information, ask your doctor or pharmacist.
Call your doctor for medical advice about side effects. You may report side effects to FDA at 1-800-FDA-1088.

How should I store OFEV?

- Store OFEV at room temperature between 68°F to 77°F (20°C to 25°C).
- Keep OFEV dry and protect from high heat.

Keep OFEV and all medicines out of the reach of children.

General information about the safe and effective use of OFEV.
Medicines are sometimes prescribed for purposes other than those listed in a Patient Information leaflet. Do not use OFEV for a condition for which it was not prescribed. Do not give OFEV to other people, even if they have the same symptoms you have. It may harm them. This Patient Information leaflet summarizes the most important information about OFEV. If you would like more information, talk to your doctor. You can ask your pharmacist or doctor for information about OFEV that is written for health professionals.
For more information about OFEV, including the current prescribing information, and patient support, go to www.ofev.com/support or call Boehringer Ingelheim Pharmaceuticals, Inc. at 1-800-542-6257, or scan the code to go to www.ofev.com/support.

What are the ingredients in OFEV?
Active ingredient: nintedanib
Inactive ingredients: Fill Material: hard fat, lecithin, triglycerides. Capsule Shell: ferric oxide red, ferric oxide yellow, gelatin, glycerol, titanium dioxide
Distributed by: Boehringer Ingelheim Pharmaceuticals, Inc. Ridgefield, CT 06877 USA
Licensed from: Boehringer Ingelheim International GmbH
OFEV is a registered trademark of and used under license from Boehringer Ingelheim International GmbH.
Copyright © 2025 Boehringer Ingelheim International GmbH, ALL RIGHTS RESERVED
COL13994BJ182024

This Patient Information has been approved by the U.S. Food and Drug Administration.

Revised: May 2025

PRINCIPAL DISPLAY PANEL - 150 mg Capsule Bottle Carton

NDC 0597-0145-60

Ofev®
(nintedanib
capsules)

150 mg*

Rx only

60 capsules

Boehringer
Ingelheim

PRINCIPAL DISPLAY PANEL - 100 mg Capsule Bottle Carton

NDC 0597-0143-60

Ofev®
(nintedanib capsules)

100 mg*

Rx only

60 capsules

Boehringer
Ingelheim